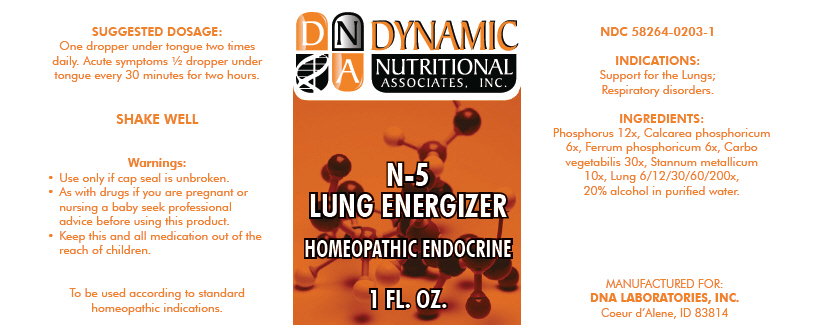 DRUG LABEL: N-5
NDC: 58264-0203 | Form: SOLUTION
Manufacturer: DNA Labs, Inc.
Category: homeopathic | Type: HUMAN OTC DRUG LABEL
Date: 20250109

ACTIVE INGREDIENTS: PHOSPHORUS 12 [hp_X]/1 mL; TRIBASIC CALCIUM PHOSPHATE 6 [hp_X]/1 mL; FERROSOFERRIC PHOSPHATE 6 [hp_X]/1 mL; ACTIVATED CHARCOAL 30 [hp_X]/1 mL; TIN 10 [hp_X]/1 mL; BEEF LUNG 200 [hp_X]/1 mL
INACTIVE INGREDIENTS: ALCOHOL; WATER

N-5

NDC 58264-0203-1

PURPOSE

INDICATIONS

Support for the Lungs; Respiratory disorders.

ACTIVE INGREDIENT

INGREDIENTS

Phosphorus 12x, Calcarea phosphoricum 6x, Ferrum phosphoricum 6x, Carbo vegetabilis 30x, Stannum metallicum 10x, Lung 6/12/30/60/200x, 20% alcohol in purified water.

SUGGESTED DOSAGE

One dropper under tongue two times daily. Acute symptoms ½ dropper under tongue every 30 minutes for two hours.

STORAGE AND HANDLING

SHAKE WELL

Warnings

- Use only if cap seal is unbroken.

PREGNANCY OR BREAST FEEDING

- As with drugs if you are pregnant or nursing a baby seek professional advice before using this product.

KEEP OUT OF REACH OF CHILDREN

- Keep this and all medication out of the reach of children.

To be used according to standard homeopathic indications.

PRINCIPAL DISPLAY PANEL - 1 FL. OZ. Bottle Label

DYNAMIC
NUTRITIONAL
ASSOCIATES, INC.

N-5
LUNG ENERGIZER

HOMEOPATHIC ENDOCRINE

1 FL. OZ.